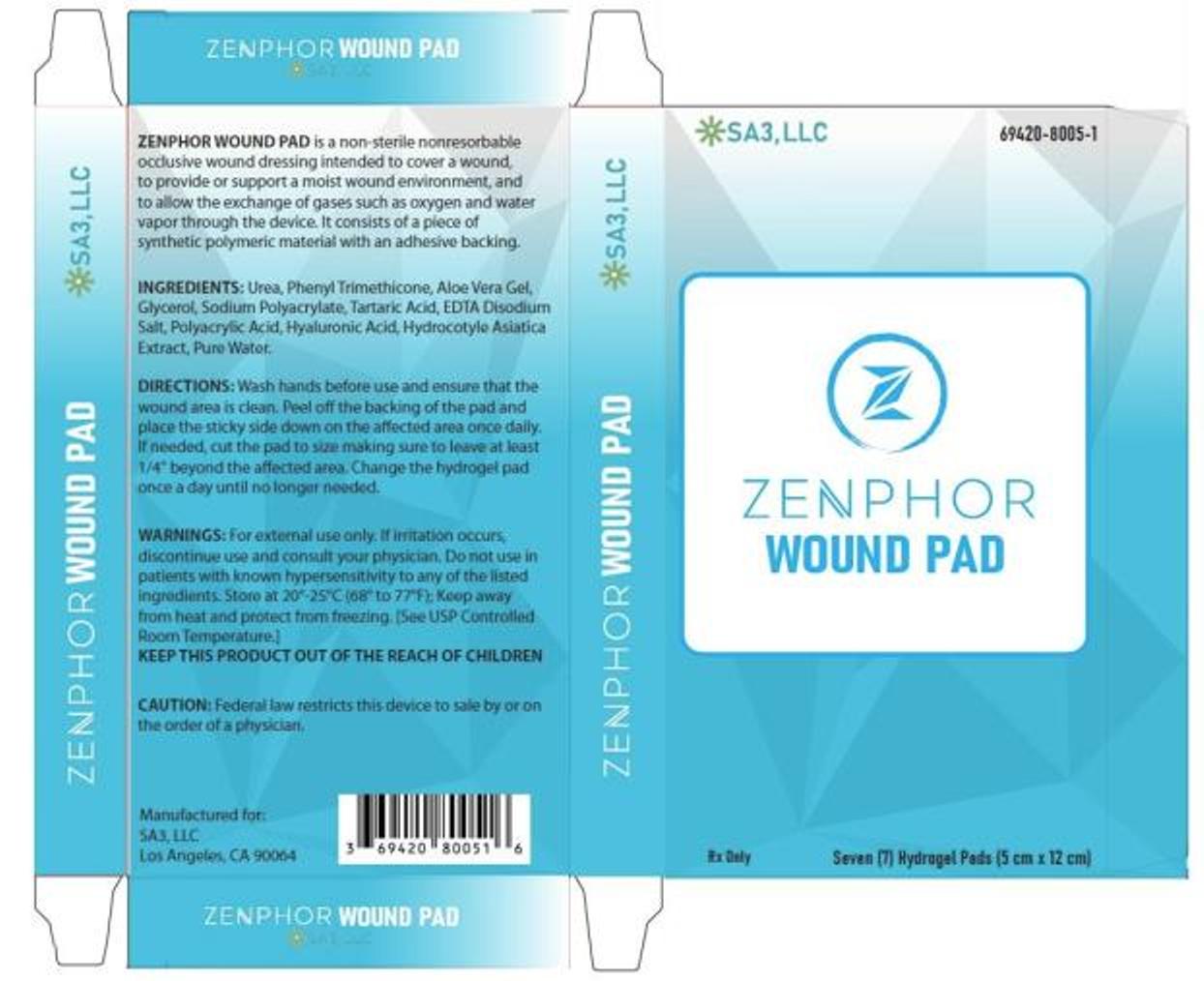 DRUG LABEL: Zenphor Wound Pad
NDC: 71073-212 | Form: PATCH
Manufacturer: Beijing HKKY Medical Tech. Co., Ltd.
Category: other | Type: MEDICAL DEVICE
Date: 20211014

71073_212_Zenphor Wound Pad

Description

ZENPHOR WOUND PAD is a non-sterile nonresorbable occlusive wound dressing intended to cover a wound, to provide or support a moist wound environment, and to allow the exchange of gases such as oxygen and water vapor through the device. It consists of a piece of synthetic polymeric material with an adhesive backing. This classification does not include an occlusive wound dressing that contains added drugs such as antimicrobial agents, added biologics such as growth factors, or is composed of materials derived from animal sources.

Each ZENPHOR WOUND PAD contains: Urea, Phenyl Trimethicone, Aloe Vera Gel, Glycerol, Sodium Polyacrylate, Tartaric Acid, EDTA Disodium Salt, Polyacrylic Acid, Hyaluronic Acid, Hydrocotyle Asiatica Extract, and Water.

INDICATIONS AND USES

It is intended to provide a moist wound healing environment to facilitate the normal wound healing process.

Contraindications

ZENPHOR WOUND PAD is contraindicated in patients with known hypersensitivity to any of the listed ingredients.

Warnings

For external use only. If irritation occurs, discontinue use and consult your physician. Do not use in patients with known hypersensitivity to any of the listed ingredients. Store at 20°-25°C (68° to 77°F); Keep away from heat and protect from freezing. [See USP Controlled Room Temperature.]

KEEP THIS PRODUCT OUT OF THE REACH OF CHILDREN

Precautions

Stop use and ask a doctor if irritation develops. In rare instances, silicone sheets may cause a rash on the skin. If ingested, get medical help or contact Poison Control Center right away.
This medication should be used as directed by your physician during pregnancy or while breastfeeding. Consult your doctor about the risks and benefits.

CAUTION: Federal law restricts this device to sale by or on the order of a physician.

Adverse Reactions

On rare occasions, the pads may cause temporary redness, stinging, burning or irritation and normally disappear when the medication is discontinued.

Dosage and Administration

Wash hands before use and ensure that the wound area is clean. Peel off the backing of the pad and place the sticky side down on the affected area once daily. If needed, cut the pad to size making sure to leave at least 1/4" beyond the affected area. Change the hydrogel pad once a day until no longer needed.

How is ZENPHOR WOUND PAD Supplied

ZENPHOR WOUND PAD is supplied in:
Seven (7) Non-Sterile Hydrogel Pads – in 1 Carton
69420-8005-1

Store at 20°-25°C (68° to 77°F); Keep away from heat and protect from freezing. [See USP Controlled Room Temperature.]
Manufactured for:
SA3, LLC
Los Angeles, CA 90064